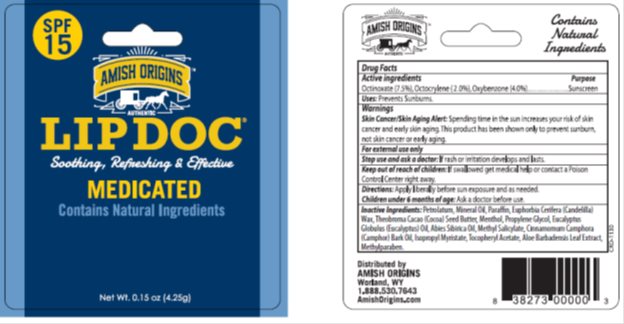 DRUG LABEL: Amish Origins SPF 15 Lip Balm
NDC: 62212-350 | Form: STICK
Manufacturer: Amish Origins
Category: otc | Type: HUMAN OTC DRUG LABEL
Date: 20170406

ACTIVE INGREDIENTS: OCTINOXATE 7.5 mg/1 g; OXYBENZONE 4.0 mg/1 g; OCTOCRYLENE 2.0 mg/1 g
INACTIVE INGREDIENTS: PETROLATUM 27.0 mg/1 g; LIGHT MINERAL OIL 25.5 mg/1 g; .ALPHA.-TOCOPHEROL ACETATE .29 mg/1 g; CANDELILLA WAX 8.0 mg/1 g; MENTHOL, (+)- 2.0 mg/1 g

Drug Facts

Active ingredient

Octinoxate (7.5%), Octocrylene (2.0%), Oxybenzone (4.0%)

Purpose

Sunscreen, Sunscreen, Sunscreen

Keep Out of Reach of Children

If swallowed get medical help or contact a Poison Control Center right away.

Uses

Prevents Sunburns

Warnings

Skin Cancer/Skin Aging Alert: Spending time in the sun increases your risk of skin cancer and early skin aging. This product has been shown only to prevent sunburn, not skin cancer or early aging.

For external use only: Stop use and ask a doctor: if rash or irritation develops and lasts.

Directions

Apply liberally before sun exposure and as needed. Children under 6 months of age: Ask a doctor before use.

Inactive Ingredients

Petrolatum, Mineral Oil, Paraffin, Euphorbia Cerifera (Candelilla) Wax, Theobroma Cacao (Cocoa) Seed Butter, Menthol, Propylene Glycol, Eucalyptus Globulus (Eucalyptus) Oil, Abies Sibirica Oil, Methyl Salicylate, Cinnamomum Camphora (Camphor) Bark Oil, Isopropyl Myristate, Tocopheryl Acetate, Aloe Barbadenis Leaf Extract, Paraffin, Methylparaben.